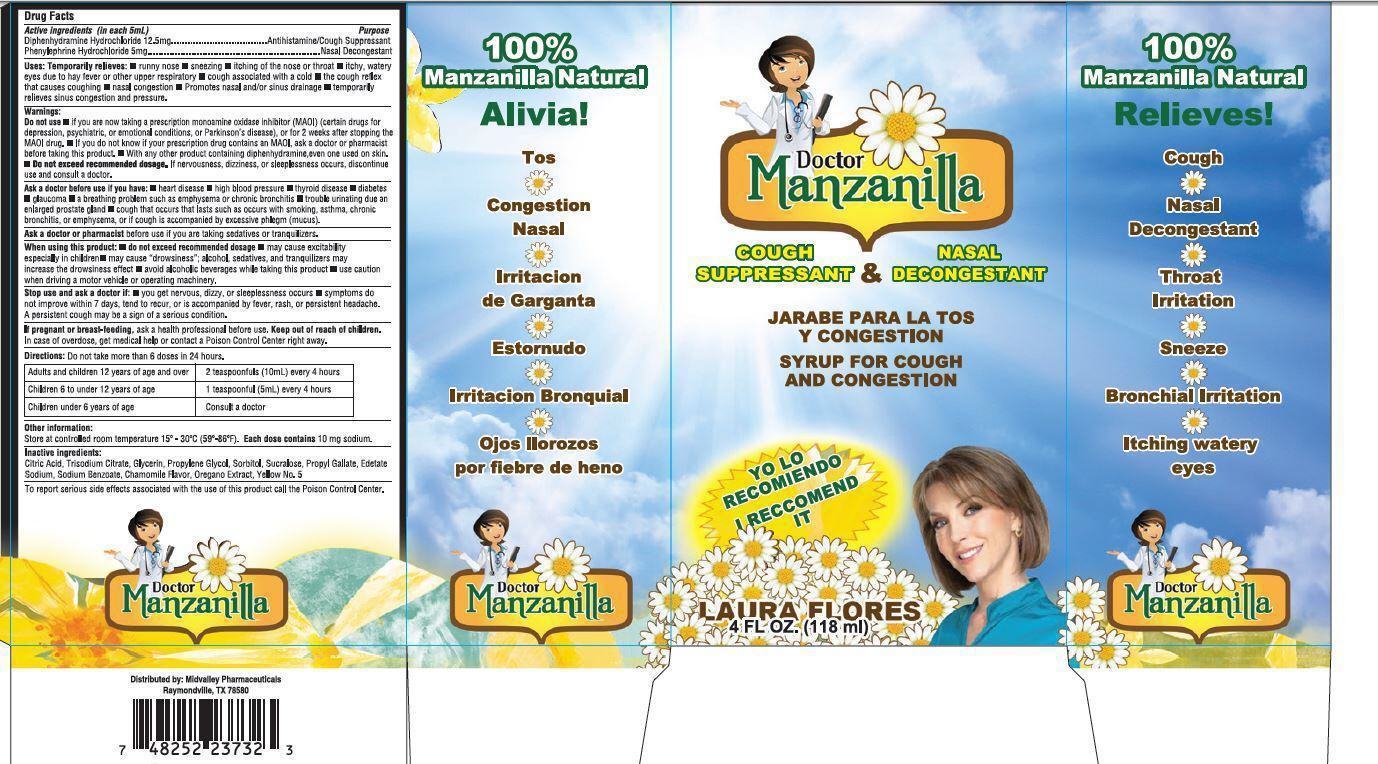 DRUG LABEL: Doctor Manzanilla Cough Suppressant and Nasal Decongestant
NDC: 62558-001 | Form: SOLUTION
Manufacturer: Mid Valley Pharmaceuticals LLC
Category: otc | Type: HUMAN OTC DRUG LABEL
Date: 20150629

ACTIVE INGREDIENTS: DIPHENHYDRAMINE HYDROCHLORIDE 12.5 mg/5 mL; PHENYLEPHRINE HYDROCHLORIDE 5 mg/5 mL
INACTIVE INGREDIENTS: CITRIC ACID MONOHYDRATE; SODIUM CITRATE; GLYCERIN; PROPYLENE GLYCOL; SORBITOL; SUCRALOSE; PROPYL GALLATE; EDETATE SODIUM; SODIUM BENZOATE

Doctor Manzanilla Cough Suppressant and Nasal Decongestant

Drug Facts

Active ingredients (in each 5mL)

Diphenhydramine Hydrochloride 12.5mg

Phenylephrine Hydrochloride 5mg

Purpose

Antihistamine/Cough Suppressant

Nasal Decongestant

Uses:

Temporarily relieves

- runny nose
- sneezing
- itching of the nose or throat
- itchy, watery eyes due to hay fever or other upper respiratory
- cough associated with a cold
- the cough reflex that causes coughing
- nasal congestion
- Promotes nasal and/or sinus drainage
- temporarily relieves sinus congestion and pressure.

Warnings:

Do not use

- if you are now taking a prescription monoamine oxidase inhibitor (MAOI) (certain drugs for depression, psychiatric, or emotional conditions, or Parkinson's disease), or for 2 weeks after stopping the MAOI drug.
- If you do not know if your prescription drug contains an MAOI, ask a doctor or pharmacist before taking this product.
- With any other product containing diphenhydramine,even one used on skin.
- Do not exceed recommended dosage.
- If nervousness, dizziness, or sleeplessness occurs, discontinue use and consult a doctor.

Ask a doctor before use if you have

- heart disease
- high blood pressure
- thyroid disease
- diabetes
- glaucoma
- a breathing problem such as emphysema or chronic bronchitis
- trouble urinating due an enlarged prostate gland
- cough that occurs that lasts such as occurs with smoking, asthma, chronic bronchitis, or emphysema, or if cough is accompanied by excessive phlegm (mucus).

Ask a doctor or pharmacist

before use if you are taking sedatives or tranquilizers

When using this product:

- do not exceed recommended dosage
- may cause excitability especially in children
- may cause "drowsiness"; alcohol, sedatives, and tranquilizers may increase the drowsiness effect
- avoid alcoholic beverages while taking this product
- use caution when driving a motor vehicle or operating machinery.

Stop use and ask a doctor if:

- you get nervous, dizzy, or sleeplessness occurs
- symptoms do not improve within 7 days, tend to recur, or is accompanied by fever, rash, or persistent headache. A persistent cough may be a sign of a serious condition.

If pregnant or breast-feeding,

ask a health professional before use.

Keep out of reach of children.

In case of overdose, get medical help or contact a Poison Control Center right away.

Directions:

Do not take more than 6 doses in 24 hours.

Adults and children 12 years of age and over | 2 teaspoonfuls (10mL) every 4 hours
Children 6 to under 12 years of age | 1 teaspoonfuls (5mL) every 4 hours
Children under 6 years of age | Consult a doctor

Other information:

Store at controlled room temperature 15º - 30ºC (59º-86ºF). Each dose contains 10 mg sodium.

Inactive ingredients:

Citric Acid, Trisodium Citrate, Glycerin, Propylene Glycol, Sorbitol, Sucralose, Propyl Gllate, Edetate Sodium, Sodium Benzoate, Chamomile Flavor, Oregano Extract, Yellow No. 5

ADVERSE REACTIONS

To report serious side effects associated with the use of this product call the Poison Control Center.

Package Label

Doctor Manzanilla

COUGH SUPPRESSANT & NASAL DECONGESTANT

I RECCOMEND IT

LAURA FLORES
4 FL OZ. (118 ml)

100%
Manzanilla Natural

Relieves!

Cough

Nasal

Decongestant

Throat

Irritation

Sneeze

Bronchial Irritation

Itching watery eyes

Distributed by: Midvalley Pharmaceuticals
Raymondville, TX 78580

7 48252 23732 3